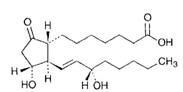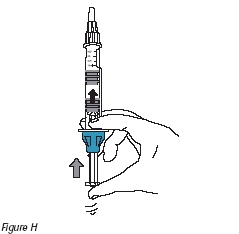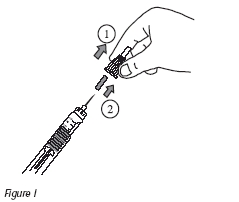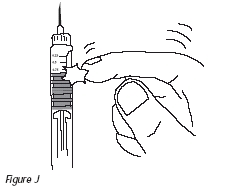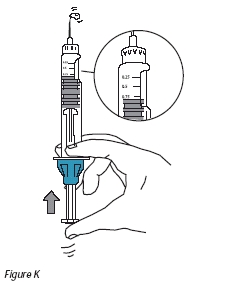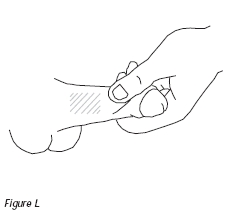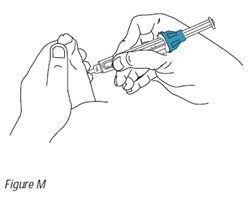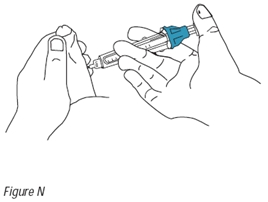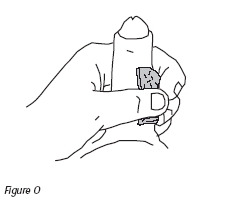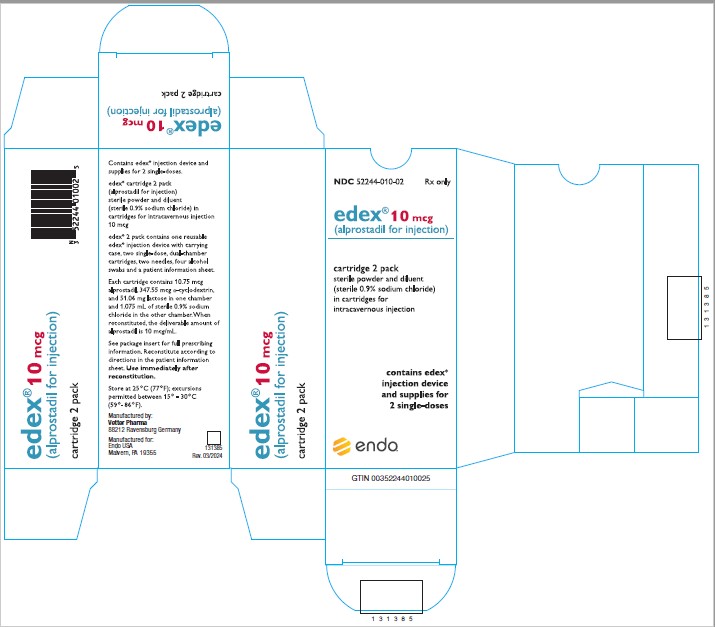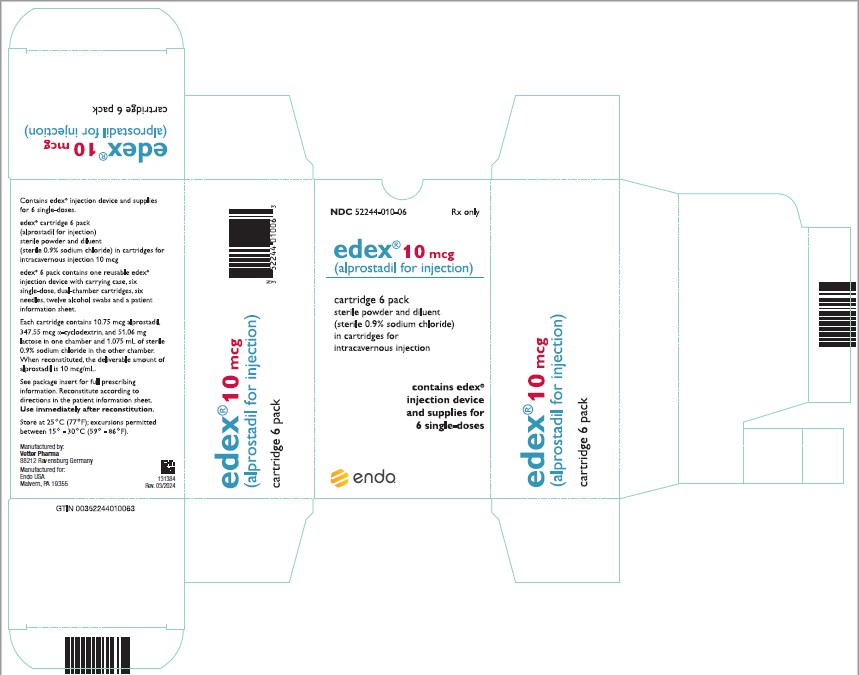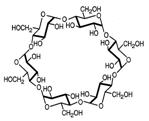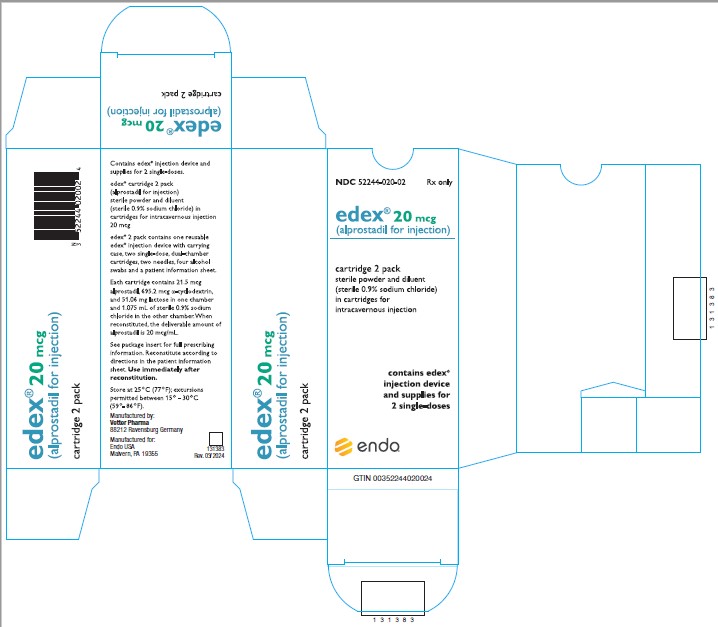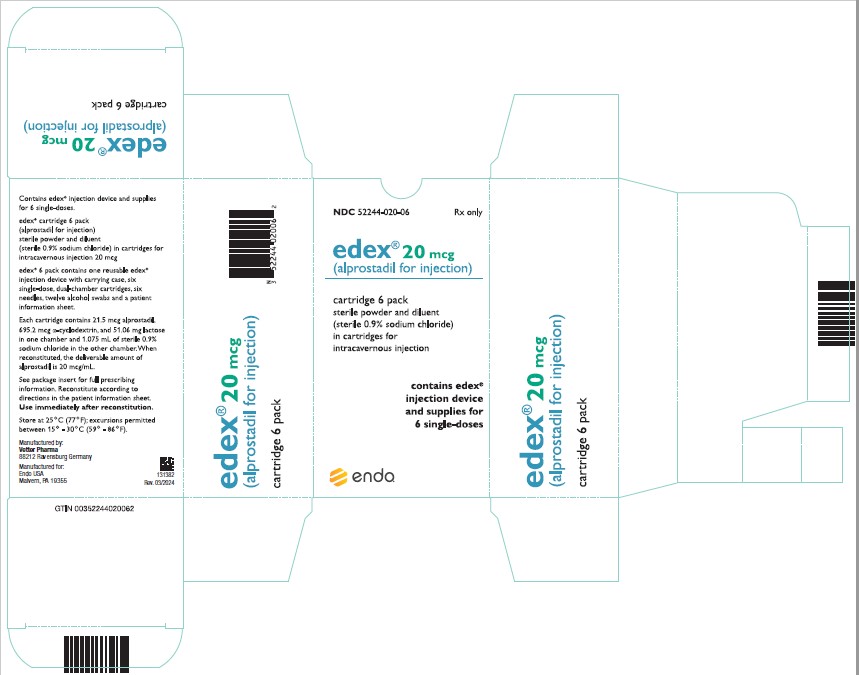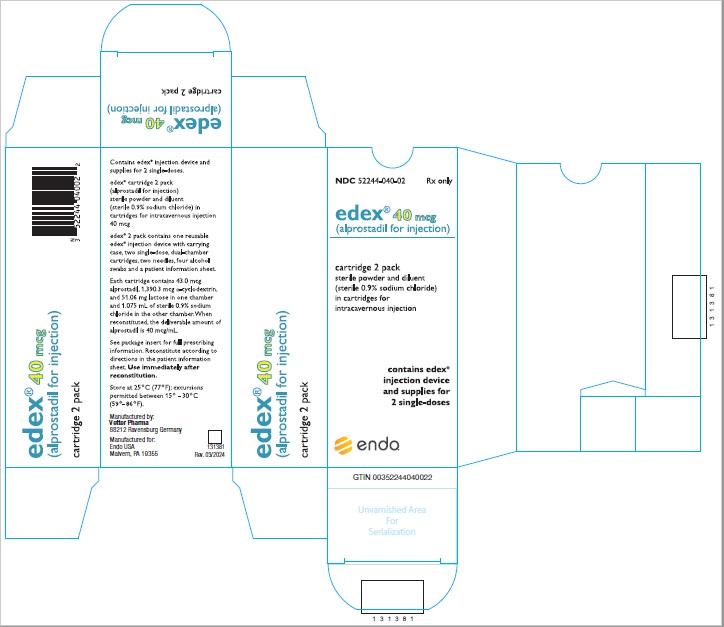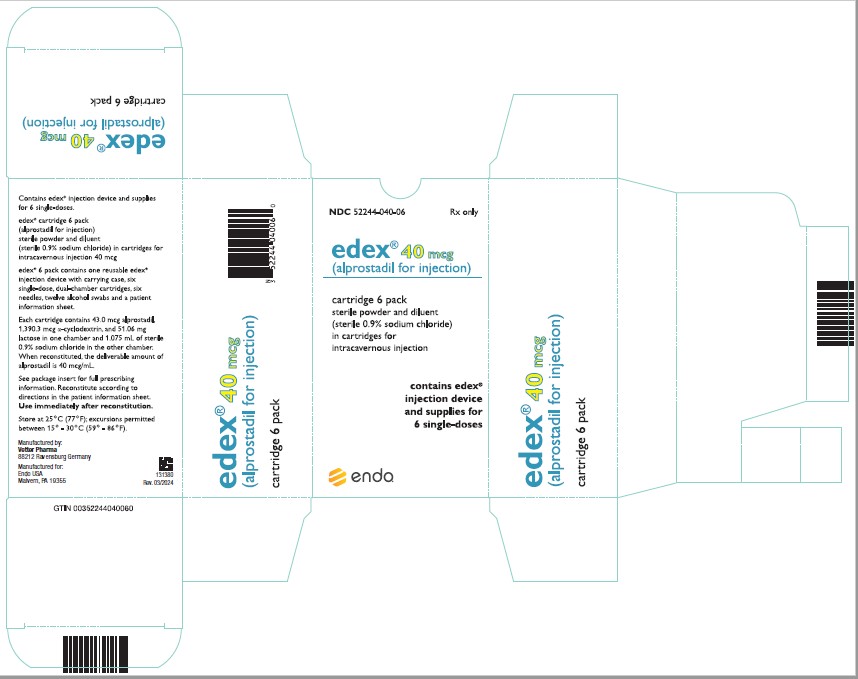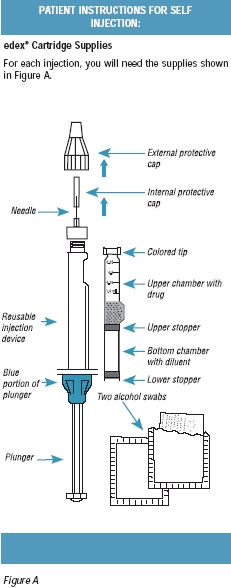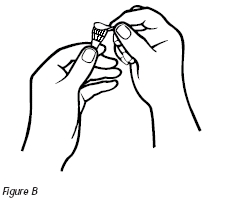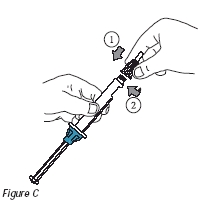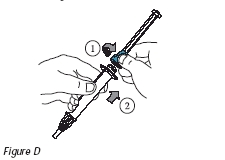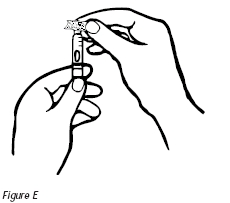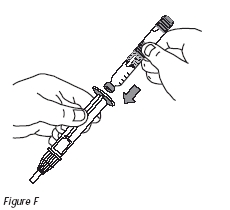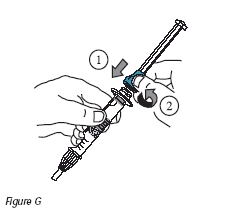 DRUG LABEL: Edex
NDC: 52244-010 | Form: INJECTION, POWDER, LYOPHILIZED, FOR SOLUTION
Manufacturer: ENDO USA, Inc.
Category: prescription | Type: HUMAN PRESCRIPTION DRUG LABEL
Date: 20240327

ACTIVE INGREDIENTS: ALPROSTADIL 10 ug/1 mL
INACTIVE INGREDIENTS: ALFADEX; LACTOSE, UNSPECIFIED FORM; SODIUM CHLORIDE; WATER

edex®
(alprostadil for injection)

For Intracavernous Use Only

Sterile Powder and Diluent
(sterile 0.9% sodium chloride) in Cartridges

Rx Only

DESCRIPTION

edex® (alprostadil for injection) is a sterile, pyrogen-free powder containing alprostadil in an alfadex (α-cyclodextrin) inclusion complex. Alprostadil is an endogenous substance known as prostaglandin E1 (PGE1). edex® is supplied in single-dose, dual-chamber cartridges.

edex® is lyophilized in single-dose, dual-chamber cartridges intended for use with the reusable edex® injection device. One chamber of the cartridge contains alprostadil, alfadex and lactose as a sterile, pyrogen-free powder. The other chamber contains 1.075 mL of sterile 0.9% sodium chloride. The edex® cartridges are supplied in three strengths: 10-mcg cartridge (10.75 mcg alprostadil, 347.55 mcg α-cyclodextrin, 51.06 mg lactose); 20-mcg cartridge (21.5 mcg alprostadil, 695.2 mcg α-cyclodextrin, 51.06 mg lactose); 40-mcg cartridge (43 mcg alprostadil, 1,390.3 mcg α-cyclodextrin, 51.06 mg lactose). The edex® injection device is used to reconstitute the sterile powder in one chamber with the sterile 0.9% sodium chloride in the other chamber. After reconstitution, the edex® injection device is used to administer the intracavernous injection of alprostadil.

The chemical name for alprostadil is (1R,2R,3R)-3-Hydroxy-2-[(E)-(3S)-3-hydroxy-1-octenyl]-5-oxocyclopentane heptanoic acid. The empirical formula is C20H34O5 and the molecular weight is 354.49. The chemical structure is:

The α-cyclodextrin inclusion complex improves the water solubility of alprostadil. The empirical formula of α-cyclodextrin is C36H60O30 and the molecular weight is 972.85.

The chemical structure is:

Alprostadil alfadex is a white, odorless, hygroscopic powder. It is freely soluble in water and practically insoluble in ethanol, ethyl acetate and ether. After reconstitution, the active ingredient, alprostadil, immediately dissociates from the α-cyclodextrin inclusion complex. The reconstituted solution is clear and colorless and has a pH between 4.0 and 8.0. When the single-dose, dual-chamber cartridge containing either 10.75, 21.5, or 43 mcg of alprostadil is placed into the edex® injection device and reconstituted, the deliverable amount of alprostadil in each milliliter is 10, 20 or 40 mcg, respectively.

CLINICAL PHARMACOLOGY

Alprostadil (PGE1) is one of the prostaglandins, a family of naturally occurring acidic lipids with various pharmacological effects. Endogenous PGE1 is derived from dihomo-gamma-linolenic acid, a fatty acid found within the phospholipids of cellular membranes. As an endogenous substance, PGE1 exerts its biological effects either directly or indirectly by regulating and modifying the synthesis and effects of other hormones and mediators.

Mode of Action

Alprostadil is a smooth muscle relaxant. Precontracted isolated preparations of the human corpus cavernosum, corpus spongiosum and cavernous artery are relaxed by alprostadil. Alprostadil has been shown to bind to specific receptors in human penile tissue. Two types of receptors that differ in their PGE1 binding affinity have been identified. The binding of alprostadil to its receptors is accompanied by an increase in intracellular cAMP levels. Human cavernous smooth muscle cells respond to alprostadil by releasing intracellular calcium into the surrounding medium. Smooth muscle relaxation is associated with a reduction of the cytoplasmic free calcium concentration. Alprostadil also attenuates presynaptic noradrenaline release in the corpus cavernosum which is essential for the maintenance of a flaccid and non-erect penis.

Alprostadil induces erection by relaxation of trabecular smooth muscle and by dilation of cavernous arteries. This leads to expansion of lacunar spaces and entrapment of blood by compressing the venules against the tunica albuginea, a process referred to as the corporal veno-occlusive mechanism.

Pharmacokinetics

Alpha-Cyclodextrin

After reconstitution, PGE1 immediately dissociates from the α-cyclodextrin inclusion complex; the in vivo disposition of both components occurs independently after administration. After intravenous infusion of radiolabeled α-cyclodextrin to healthy volunteers, the radiolabeled components were rapidly eliminated within 24-hours, urine accounting for 81% to 83% of radioactivity and feces for 0.1%. There was no evidence of significant accumulation of radiolabeled α-cyclodextrin in the body even after 7 days of repeated intravenous injection. After intracavernous administration in monkeys, radiolabeled α-cyclodextrin was rapidly distributed from the injection site with less than 0.1% of the dose remaining in the penis 1 hour after administration. There was no evidence of tissue retention of radiolabeled α-cyclodextrin in monkeys.

Alprostadil

Absorption

After intracavernous injection of 20 mcg of edex® in 24 patients with erectile dysfunction, mean systemic plasma concentrations of PGE1 increased from baseline of 0.8 ± 0.6 pg/mL to a peak (Cmax) of 16.8 ± 18.9 pg/mL (corrected for baseline) within 2 to 5 minutes and dropped to endogenous plasma levels within 2 hours (Table 1). The absolute bioavailability of alprostadil estimated from systemic exposure was about 98% as compared to the same dose given by a short-term intravenous infusion.

Distribution

The volume of distribution for PGE1 was not estimated. Approximately 93% of PGE1 found in plasma is protein-bound.

Metabolism

PGE1 is metabolized in the corpus cavernosum after intracavernous administration. PGE1 entering the systemic circulation is rapidly and extensively metabolized in the lungs with a first-pass pulmonary elimination of 60 to 90% of PGE1. Enzymatic oxidation of the C15-hydroxy group followed by reduction of the C13, 14-double bond produces the primary metabolites, 15-keto-PGE1, 15-keto-PGE0, and PGE0. 15-keto-PGE1 has only been detected in vitro in homogenized lung preparations, whereas 15-keto-PGE0 and PGE0 have been measured in plasma. Unlike the 15-keto metabolites which are less pharmacologically active than the parent compound, PGE0 is similar in potency to PGE1 in vitro using isolated animal organs.

After intracavernous injection of 20 mcg of edex® to 24 patients with erectile dysfunction, mean systemic plasma 15-keto-PGE0 levels increased within 7 minutes from endogenous levels of 12.9 ± 11.8 pg/mL to a Cmax of 421 ± 337 pg/mL (corrected for baseline) followed by a decrease to baseline levels in several hours. Mean systemic plasma PGE0 levels increased within 20 minutes from endogenous levels of 0.6 ± 0.5 pg/mL to a Cmax of 3.9 ± 2.3 pg/mL (corrected for baseline) followed by a decrease to baseline levels in several hours.

Excretion

After further degradation of PGE1 by beta and omega oxidation, the main metabolites are excreted primarily in urine (88%) and feces (12%) over 72 hours, and total excretion is essentially complete (92%) within 24 hours after administration. No unchanged PGE1 has been found in the urine and there is no evidence of tissue retention of PGE1 and its metabolites. After intracavernous injection of 20 mcg of edex® in patients with erectile dysfunction, the terminal half-lives (t½) of 15-keto-PGE0 and PGE0 were calculated to be 40.9 ± 16.5 minutes and 63.2 ± 31.1 minutes, respectively. The terminal half-life of PGE1 in healthy volunteers was calculated to be around 9 to 11 minutes which is consistent with that reported in the literature (8 minutes).

Mean total body clearance of PGE1 in patients with erectile dysfunction was calculated to be around 115 L/min after an intravenous infusion of 20 mcg alprostadil. The above value exceeded cardiac output indicating extensive and rapid elimination of PGE1 in the lungs and/or blood.

Special Populations

Geriatric: The potential effect of age on the pharmacokinetics of alprostadil has not been formally evaluated.

Race: The potential influence of race on the pharmacokinetics of alprostadil has not been formally evaluated.

Hepatic Insufficiency

In a study in symptomatic subjects with impaired hepatic function and age/weight/sex-matched healthy volunteers, 120 mcg of alprostadil was administered by intravenous infusion over 2 hours. The mean Cmax value of PGE1 in hepatically impaired patients was 96% higher than in healthy volunteers. Mean Cmax values of both 15-keto-PGE0 and PGE0 increased 65% as compared to those in healthy volunteers. The terminal half-lives of PGE1, PGE0, and 15-keto-PGE0 and plasma albumin levels were similar in patients compared to healthy volunteers. Due to the fact that PGE1 is primarily metabolized in the lung, the observed differences between hepatically impaired subjects and healthy volunteers were not anticipated; the mechanism responsible for the observed discrepancies is not known.

Renal Impairment

In a study in symptomatic subjects with end-stage renal disease undergoing hemodialysis and age/weight/sex-matched healthy volunteers, 120 mcg of alprostadil was administered by intravenous infusion over 2 hours. The mean Cmax value of PGE1 in renally impaired patients was 37% lower as compared to that in healthy volunteers whereas mean Cmax values of 15-keto-PGE0 and PGE0 in these patients increased 104% and 145%, respectively, as compared to those in healthy volunteers. The terminal half-lives of PGE1, PGE0, and 15-keto-PGE0 and plasma albumin levels were similar in these patients vs healthy volunteers. The mechanism responsible for the observed discrepancies between renally impaired subjects and healthy volunteers is not known.

Pulmonary Disease

The pulmonary extraction of alprostadil following intravascular administration was reduced by 15% (66 ± 3.6% vs 78 ± 2.3%) in patients with acute respiratory distress syndrome (ARDS) compared with a group of patients with normal respiratory function who were undergoing cardiopulmonary bypass surgery. Pulmonary clearance was found to vary as a function of cardiac output and pulmonary intrinsic clearance in a group of 14 patients with ARDS or at risk of developing ARDS following trauma or sepsis. In this study, the pulmonary extraction efficiency of alprostadil ranged from subnormal (11%) to normal (90%), with an overall mean of 67%.

Drug-Drug Interactions

In clinical trials, concomitant use of agents such as antihypertensive drugs, diuretics, antidiabetic agents (including insulin), or nonsteroidal anti-inflammatory drugs had no apparent effect on the efficacy or safety of edex®.

Aspirin, Warfarin, Digoxin, Glyburide

Several drug-drug interaction studies have been conducted with alprostadil alone or in combination with aspirin, digoxin or warfarin in healthy volunteers and with glyburide in subjects with stable, non-insulin dependent diabetes mellitus. The pharmacokinetic profiles of aspirin, warfarin, digoxin, and glyburide were not affected by concomitant administration of alprostadil. There were no clinically important changes or trends in pharmacodynamic parameters for these drugs.

Heparin

The pharmacokinetic and pharmacodynamic interaction between alprostadil intravenous infusion, 90 mcg over 3 hours, and heparin (5,000 IU) was evaluated in 12 healthy volunteers. Alprostadil had a significant effect on the pharmacodynamics of heparin resulting in a 140% increase in partial thromboplastin time and a 120% increase in thrombin time. Therefore, caution should be exercised with concomitant administration of heparin and edex®.

Table 1
Study No. | Participants | Route and Dose Administration | Drug/ Metabolites | Cmax^1 (pg/mL) | Tmax (min) | AUC^2 (pg∙min/mL) | Total Clearance^3 (L/min) | t1/2^4 (min)
PHAKI 848 | Erectile Dysfunction Patients | 20 mcg/0.5 hr IV | PGE1 | 7.09 ± 3.12 | 25.5 ± 4.8 | 174 ± 101 | 115 | ---
PHAKI 848 | Erectile Dysfunction Patients | 20 mcg/0.5 hr IV | 15-keto- PGE0 | 471 ± 88 | 30.0 ± 1.2 | 13705 ± 2559 | --- | 15.6 ± 5.6
PHAKI 848 | Erectile Dysfunction Patients |  | PGE0 | 7.10 ± 2.19 | 32.2 ± 2.4 | 380 ± 115 | --- | 39.8 ± 26.3
PHAKI 848 | Erectile Dysfunction Patients | 20 mcg/IC | PGE1 | 16.8 ± 18.9 | 4.8 ± 3.3 | 173 ± 115 | --- | ---
PHAKI 848 | Erectile Dysfunction Patients |  | 15-keto- PGE0 | 421 ± 337 | 9.7 ± 7.7 | 10500 ± 4101 | --- | 40.9 ± 16.5
PHAKI 848 | Erectile Dysfunction Patients |  | PGE0 | 3.9 ± 2.3 | 20.3 ± 12.6 | 252 ± 134 | --- | 63.2 ± 31.1
^1 Baseline-corrected data.
^2 AUC0-150 for intravenous (IV) infusion and AUC0-120 for intracavernous (IC) injection.
^3 Calculated as IV dose/AUC0-150 (IV).
^4 Apparent terminal half-life

Clinical Studies

In two studies (protocol numbers KU-620-001 [Study 1] and KU-620-002 [Study 2]), the safety and efficacy of edex® were evaluated in 347 men with a diagnosis of erectile dysfunction due to vasculogenic, neurogenic and/or mixed etiology. Each study consisted of three phases: an in-office dose-titration phase, a two-week double-blind cross-over phase at home, and an open-label at home treatment phase that lasted for 12 months (Study 1) or six months (Study 2).

During the dose-titration phase, individualized optimum doses of edex® were established. Erectile response was measured by the Buckling Test to assess axial penile rigidity. A positive Buckling Test was achieved if the erect penis was able to support an axial load of 1.0 kg without buckling of the penile shaft. During the subsequent two-week double-blind, cross-over phase, patients self-injected edex® or placebo at home. Thereafter, patients continued to perform self-injections of open-label edex® for six or 12 months, and the occurrence of an erection sufficient for sexual intercourse was documented following each injection.

Results

Study 1: One hundred fourteen men with a mean age of 53 years (range 22 to 65 years) were enrolled in the first phase. The mean optimum dose was 13.8 mcg (range 1 to 20 mcg). Seventy-six percent (87/114) of patients had an erection with a positive penile Buckling Test. Among the 71% (81/114) of patients who entered the placebo-controlled phase, an erection sufficient for sexual intercourse was achieved in 74% (60/81) of patients following edex® injection compared to 7% (6/81) of patients following placebo injection. The mean duration of erection following edex® was 56.9 minutes compared to 4.0 minutes following placebo. Among the 65% (74/114) of patients who entered the open-label treatment phase, the mean rate of response with an erection sufficient for sexual intercourse was 88.9% through 12 months. The average dose of edex® remained essentially unchanged throughout the study duration.

Study 2: Two hundred thirty-three men with a mean age of 59.8 years (range 23 to 74 years) were enrolled in the first phase. The mean optimum dose was 25.9 mcg (range 1 to 40 mcg). Seventy-three percent (171/233) of patients had an erection with a positive penile Buckling Test. Among the 60% (141/233) of patients who entered the placebo-controlled phase, an erection sufficient for sexual intercourse was achieved in 73% (103/141) of patients following edex® injection compared to 13% (18/141) of patients following placebo injection. The mean duration of erection following edex® was 59.0 minutes compared to 7.6 minutes following placebo. Among the 60% (139/233) of patients who entered the open-label treatment phase, the mean rate of response with an erection sufficient for intercourse was 85.3% through six months. The average dose of edex® remained essentially unchanged throughout the study duration.

INDICATIONS AND USAGE

edex® is indicated for the treatment of erectile dysfunction due to neurogenic, vasculogenic, psychogenic, or mixed etiology.

CONTRAINDICATIONS

edex®should not be used:

- in men who have conditions that predispose them to priapism, such as sickle cell anemia or sickle cell trait, multiple myeloma, or leukemia (see WARNINGS).
- for the treatment of erectile dysfunction in men with fibrotic conditions of the penis, such as cavernosal fibrosis or Peyronie’s disease (see PRECAUTIONS).
- in men with penile implants

WARNINGS

Prolonged erections greater than four hours in duration occurred in 4% of all patients treated up to 24 months. The incidence of priapism (erections greater than 6 hours in duration) was <1% with long-term use for up to 24 months. In the majority of cases, spontaneous detumescence occurred. Pharmacologic intervention and/or aspiration of blood from the corpora was necessary in 1.6% of 311 patients with prolonged erections/priapism. To minimize the chances of prolonged erection or priapism, edex® should be titrated slowly to the lowest effective dose (see DOSAGE AND ADMINISTRATION). The patient must be instructed to immediately report to his prescribing physician or, if unavailable, to seek immediate medical assistance for any erection that persists longer than six hours. If priapism is not treated immediately, penile tissue damage and permanent loss of potency may result.

PRECAUTIONS

General

1) Intracavernous injections of edex® can lead to increased peripheral blood levels of PGE1 and its metabolites, especially in those patients with significant corpora cavernosa venous leakage. Increased peripheral blood levels of PGE1 and its metabolites may lead to hypotension and/or dizziness.

2) Regular follow-up of patients, with careful examination of the penis at the start of therapy and at regular intervals (e.g. 3 months), is strongly recommended to identify any penile changes. The overall incidence of penile fibrosis, including Peyronie's disease, reported in clinical studies up to 24 months with edex® was 7.8%. Treatment with edex® should be discontinued in patients who develop penile angulation, cavernosal fibrosis, or Peyronie's disease. Treatment can be resumed if the penile abnormality subsides.

3) The safety and efficacy of combinations of edex® and other vasoactive agents have not been systematically studied. Therefore, the use of such combinations is not recommended.

4) After injection of the edex® solution, compression of the injection site for five minutes, or until bleeding stops, is necessary. Patients on anticoagulants, such as warfarin or heparin, may have increased propensity for bleeding after intracavernous injection.

5) Underlying treatable medical causes of erectile dysfunction should be diagnosed and treated prior to initiation of therapy with edex®.

6) edex® uses a superfine (29 gauge) needle. As with all superfine needles, the possibility of needle breakage exists. Careful instruction in proper patient handling and injection techniques may minimize the potential for needle breakage.

7) The patient should be instructed not to reuse or to share needles or cartridges. As with all prescription medicines, the patient should not allow anyone else to use his medicine.

8) Cardiovascular Risk Related to Underlying Medical Conditions

There is a potential for cardiac risk of sexual activity in patients with preexisting cardiovascular disease. Therefore, treatments for erectile dysfunction, including edex®, generally should not be used in men for whom sexual activity is inadvisable because of their underlying cardiovascular status. In addition, the evaluation of erectile dysfunction should include a determination of potential underlying causes and the identification of appropriate treatment following a complete medical assessment.

Drug Interactions

The pharmacodynamic interaction between heparin (5,000 units) and alprostadil intravenous infusion (90 mcg over 3 hours) was investigated. The results indicate significant changes in partial thromboplastin time (140% increase) and thrombin time (120% increase). Therefore, caution should be exercised with concomitant administration of heparin and edex®.

(Also, see Drug-Drug Interactions in CLINICAL PHARMACOLOGY, Pharmacokinetics.)

Information for Patients

To ensure safe and effective use of edex®, the patient should be thoroughly instructed and trained in the self-injection technique before he begins intracavernous treatment with edex® at home. The desirable dose should be established in the physician's office. The instructions for preparation of the edex® solution should be carefully followed. The reconstituted solution may initially appear cloudy due to small air bubbles. Do not use the solution if it remains cloudy, contains precipitates, or is discolored. The reconstituted solution should be gently mixed, not shaken. A patient information pamphlet is included in each package of edex® cartridges.

edex® should be used immediately after reconstitution. The patient should follow the instructions in the patient information pamphlet to limit the possibility of bacterial contamination. The reconstituted cartridge is designed for one use only and should be discarded after use. The edex® cartridge contains a solid layer or Iyophilized cake of dry white powder approximately 3/8" in thickness. A normal cake may appear cracked or crumbled. If the cartridge is damaged, the cake may shrink in size. Do not use the cartridge if it appears damaged or the cake is substantially reduced in size.

If the dosage prescribed is less than 1 mL of edex® solution, excess solution will be expelled through the needle as the plunger is pushed and the upper rim of the top stopper reaches the correct volume mark for the prescribed dose. The needle must be properly discarded after use; it must not be reused or shared with other persons.

The dose of edex® that is established in the physician's office should not be changed by the patient without consulting the physician. The patient may expect an erection to occur within 5 to 20 minutes. A standard treatment goal is to produce an erection lasting no longer than 1 hour. edex® should be used no more than 3 times per week, with at least 24 hours between each use.

Patients should be aware of possible side effects of therapy with edex®; the most frequently occurring is penile pain during and/or after injection, usually mild to moderate in severity. A potentially serious adverse reaction with intracavernous therapy is priapism. Accordingly, the patient should be instructed to contact the physician's office immediately or, if unavailable, to seek immediate medical assistance if an erection persists for longer than 6 hours.

The patient should report any penile pain that was not present before or that increased in intensity, as well as the occurrence of nodules or hard tissue in the penis to his physician as soon as possible. As with any injection, infection is possible. Patients should be instructed to report to the physician any penile redness, swelling, tenderness or curvature of the erect penis. The patient must visit the physician's office for regular checkups for assessment of the therapeutic benefit and safety of treatment with edex®.

Note: Individuals who are sexually active should be counseled about the protective measures that are necessary to guard against the spread of sexually transmitted diseases, including the human immunodeficiency virus (HIV). Use of intracavernous edex® offers no protection from the transmission of sexually transmitted or blood-borne diseases. The injection of edex® can induce a small amount of bleeding at the site of injection. In patients infected with blood-borne diseases, this could increase the risk of transmission of blood-borne diseases between partners.

Carcinogenesis, Mutagenesis, Impairment of Fertility

Long-term carcinogenicity studies have not been conducted. Alprostadil showed no evidence of mutagenicity in three in vitro assays including the AMES bacterial reverse mutation assay, a forward gene mutation assay in Chinese hamster lung (V79) cells, and a chromosome aberration assay in human peripheral lymphocytes. Alprostadil did not produce damage to chromosomes or the mitotic apparatus in the in vivo rat micronucleus test.

Alprostadil did not cause any adverse effects on fertility or general reproductive performance when administered intraperitoneally to male or female rats at dose levels from 2 to 200 mcg/kg/day. The high dose of 200 mcg/kg/day is about 300 times the maximum recommended human dose (MRHD) on a body weight basis. The human dose of edex® is <1 mcg/kg (MRHD is 40 mcg and the calculation assumes a 60-kg subject).

Pregnancy, Nursing Mothers and Pediatric Use

edex® is not indicated for use in women or pediatric patients.

Geriatric Use

Of the approximately 1,065 patients who entered the in-office dose-titration period in clinical studies, 25% were 65 years or older. In clinical studies, geriatric patients required, on average, higher minimally effective doses and had a higher rate of lack of effect (optimum dose not determined). Overall differences in safety were not observed between these geriatric patients and younger patients. Geriatric patients should be dosed and titrated according to the same DOSAGE AND ADMINISTRATION recommendations as younger patients, and the lowest possible effective dose should always be used.

This drug is known to be substantially excreted by the kidney, and the risk of toxic reactions to this drug may be greater in patients with impaired renal function. Because elderly patients are more likely to have decreased renal function, care should be taken in dose selection, and it may be useful to monitor renal function.

ADVERSE REACTIONS

edex®, administered by intracavernous injection in doses ranging from 1 to 40 mcg per injection for periods up to 24 months, has been evaluated in clinical trials for safety in over 1,065 patients with erectile dysfunction. Discontinuation of therapy due to a side effect in clinical trials was required in approximately 9% of patients treated with edex® and in <1% of patients treated with placebo.

Local Adverse Reactions

The following local adverse reactions were reported in studies including 1,065 patients treated with edex® for up to two years.

Penile Pain

With use of up to 24 months, penile pain was reported at least once by 29% of patients during injection, 35% of patients during erection, and by 30% of patients after erection. On a per injection basis, 15% of injections were associated with penile pain. Penile pain was judged by patients to be mild in intensity for 80% of painful injections, moderate in intensity for 16% of painful injections, and severe in intensity for 4% of painful injections. The frequency of penile pain reports decreased over time; 41% of the patients experienced pain during the first 2 months and 3% of the patients experienced pain during months 21 to 24. In placebo-controlled studies, penile pain was reported by 31% of patients after edex® and by 9% of patients after placebo injection.

Prolonged Erection/Priapism

Prolonged erections greater than four hours in duration occurred in 4% of all patients treated up to 24 months. In placebo-controlled studies, 3% of patients treated with edex® and <1% of patients treated with placebo reported prolonged erections greater than four hours. The incidence of priapism (erections greater than 6 hours in duration) was <1% with long-term use for up to 24 months. In the majority of cases, spontaneous detumescence occurred. A higher incidence of prolonged erections was found in younger patients (<40 years), non-diabetic patients, and patients with psychogenic etiology of erectile dysfunction (See WARNINGS).

Hematoma/Ecchymosis

In patients treated with edex® for up to 24 months, local bleeding, hematoma, and ecchymosis were observed in 15%, 5%, and 4% of patients, respectively. In placebo-controlled studies, the frequency of local bleeding was 6% with injection of edex® and 3% with injection of placebo. In most cases, these reactions were attributed to faulty injection technique.

Local Adverse Reactions Reported by ≥1% of Patients
All Study Periods^1
Local Reaction | edex® | Local Reaction | edex®
 | N = 1065 |  | N = 1065
 | n (%) |  | n (%)
Penile pain during injection | 305 (29) | Ecchymosis | 44 (4)
Penile pain during erection | 368 (35) | Penile angulation | 72 (7)
Penile pain after erection | 317 (30) | Penile fibrosis | 52 (5)
Penile pain (other)^2 | 116 (11) | Cavernous body fibrosis | 20 (2)
Prolonged erection |  | Peyronie's disease | 11 (1)
> 4 ≤ 6 Hours | 44 (4) | Faulty injection technique^3 | 59 (6)
> 6 Hours | 6 (<1) | Penis disorder | 28 (3)
Bleeding | 158 (15) | Erythema | 17 (2)
Hematoma | 56 (5)
^1Protocol Numbers KU-620-001, KU-620-002, KU-620-003, F-8653.
^2Penile pain reported without an association to injection site or erection, such as pain in penis and scrotum, pain in glans penis, and burning penile pain.
^3Examples include injection into glans penis, urethra or subcutaneously.

Systemic Adverse Experiences

The following systemic adverse experiences were reported in controlled and uncontrolled studies in ≥1% of patients treated for up to 24 months with edex®.

Systemic Adverse Experiences Reported by ≥1% of Patients^1
BODY SYSTEM | edex® | BODY SYSTEM | edex® | BODY SYSTEM | edex®
Adverse Experience | N = 1065 | Adverse Experience | N = 1065 | Adverse Experience | N = 1065
Adverse Experience | n (%) | Adverse Experience | n (%) | Adverse Experience | n (%)
RESPIRATORY |  | CARDIOVASCULAR |  | UROGENITAL
Upper respiratory tract |  | Hypertension | 17 (2) | Prostate disorder | 15 (1)
infection | 58 (5) | Myocardial infarction | 13 (1) | Testicular pain | 13 (1)
Sinusitis | 14 (1) | Abnormal ECG | 12 (1) | Inguinal hernia | 11 (1)
BODY AS A WHOLE
Influenza-like symptoms | 35 (3) | METABOLIC/NUTRITIONAL |  | DERMATOLOGIC
Headache | 20 (2) | Hypertriglyceridemia | 17 (2) | Skin disorder | 14 (1)
Infection | 18 (2) | Hypercholesterolemia | 12 (1) | SPECIAL SENSES
Pain | 16 (2) | Hyperglycemia | 12 (1) | Abnormal vision | 11 (1)
MUSCULOSKELETAL
Back pain | 23 (2)
Leg pain | 13 (1)
^1Protocol Numbers KU-620-001, KU-620-002, KU-620-003, F-8653.

Hemodynamic changes, manifested as increases or decreases in blood pressure and pulse rate, were observed during clinical studies but did not appear to be dose-dependent. Four patients (<1%) reported clinical symptoms of hypotension such as dizziness or syncope.

edex® had no clinically important effect on serum or urine laboratory tests.

Post-Marketing Adverse Experiences

Needle breakage.

OVERDOSAGE

Limited data are available in regard to edex® overdose in humans. Systemic reactions are uncommon with intracavernous injection of edex®. Hypotension occurred in less than 1% of patients treated with edex®. A single dose rising tolerance study in healthy volunteers indicated that single intravenous doses of alprostadil from 1 to 120 mcg were well tolerated. Beginning with a 40 mcg bolus intravenous dose, the frequency of drug-related systemic adverse events increased in a dose-dependent manner, characterized mainly by facial flushing.

The primary symptom of an edex® overdose is a prolonged erection or priapism. Because of the potential for tissue hypoxia and possible necrosis, it is strongly recommended to treat an erection lasting more than 6 hours. The patient is strongly encouraged to go to the nearest emergency room if his personal physician is not available.

In the event of an overdose, supportive therapy according to the presence of other symptoms is recommended.

DOSAGE AND ADMINISTRATION

edex® in the Treatment of Erectile Dysfunction

The dosage range of edex® for the treatment of erectile dysfunction is 1 to 40 mcg. The intracavernous injection should be given over a 5 to 10 second interval. In a study with a dose range of 1 to 20 mcg of edex®, the mean dose was 10.7 mcg at the end of the dose titration period. In two studies with a dose range of 1 to 40 mcg of edex®, the mean dose was 21.9 mcg at the end of the dose titration period. Doses greater than 40 mcg have not been studied. A &frac12;-inch, 27- to 30-gauge needle is generally recommended for the intracavernous injection. The patient is advised not to exceed the optimum edex® dose which was determined in the doctor's office. The lowest possible effective dose should always be used.

Initial Titration in Physician's Office

Erectile Dysfunction of Vasculogenic, Psychogenic, or Mixed Etiology:

Dosage titration should be initiated at 2.5 mcg of alprostadil. If there is a partial response, the dose may be increased by 2.5 mcg to a dose of 5 mcg and then in increments of 5 to 10 mcg, depending upon erectile response, until the dose that produces an erection suitable for intercourse and not exceeding a duration of 1 hour is reached. If there is no response to the initial 2.5-mcg dose, the second dose may be increased to 7.5 mcg, followed by increments of 5 to 10 mcg. The patient must stay in the physician's office until complete detumescence occurs. If there is no response, then the next higher dose may be given within 1 hour. If there is a response, then there should be at least a 1-day interval before the next dose is given.

Erectile Dysfunction of Pure Neurogenic Etiology (Spinal Cord Injury):

Dosage titration should be initiated at 1.25 mcg of alprostadil. The dose may be increased by 1.25 mcg to a dose of 2.5 mcg, followed by an increment of 2.5 mcg to a dose of 5 mcg, and then in 5-mcg increments until the dose that produces an erection suitable for intercourse and not exceeding a duration of 1 hour is reached. The patient must stay in the physician's office until complete detumescence occurs. If there is no response, then the next higher dose may be given within 1 hour. If there is a response, then there should be at least a 1-day interval before the next dose is given.

At-Home (Maintenance Therapy) Dosing Instructions

The first injections of edex® must be done at the physician's office by medically trained personnel. Self-injection therapy by the patient can be started only after the patient is properly instructed and well trained in the self-injection technique. The physician should instruct the patient to discard any needles which become bent during the self-injection procedure as these needles may break. The physician should make a careful assessment of the patient's skills and competence with the self-injection procedure. The intracavernous injection must be done under sterile conditions. The site of injection is usually along the lateral aspect of the proximal third of the penis. Visible veins should be avoided. The side of the penis that is injected and the site of injection must be alternated. The injection site must be cleansed with an alcohol swab before injection.

The dose of edex® that is selected for self-injection treatment should provide the patient with an erection that is satisfactory for sexual intercourse and that is maintained for no longer than 1 hour. If the duration of erection is longer than 1 hour, the dose of edex® should be reduced. The lowest effective dose should be used at home. Self-injection therapy for use at home should be initiated at the dose that was determined in the physician's office. Dose adjustment may be required and should be made only after consultation with the physician.

Careful and continuous follow-up of the patient while in the self-injection program must be exercised. This is especially true for the initial self-injections, since adjustments in the dose of edex® may be needed. The recommended frequency of injection is no more than 3 times weekly, with at least 24 hours between each dose. The reconstituted edex® cartridge and needle are intended for single use only and should be discarded after use. The user should be instructed in the proper disposal of the needles and cartridges.

While on self-injection treatment, it is recommended that the patient visit the prescribing physician's office every 3 months. At that time, the efficacy and safety of the therapy should be assessed, and the dose of edex® should be adjusted, if needed.

The patient is instructed to follow the enclosed patient information pamphlet.

Preparation of Solution

The edex® injection device is used to reconstitute the single-dose, dual-chamber cartridge. The plunger is used to force the sterile 0.9% sodium chloride (1.075 mL) in one chamber into the chamber containing alprostadil. After reconstitution, the edex® injection device is used to administer the intracavernous injection of alprostadil. The reusable edex® injection device is for use only with the cartridges and needles included in the edex® Cartridge Packs.

Prepare the edex® solution immediately before use. Do not administer unless solution is clear. Do not add any drugs or solutions to the edex® solution. Discard any unused solution remaining in the cartridge. The reconstituted solution should not be stored.

The edex® cartridge contains a solid layer or lyophilized cake of dry white powder approximately 3/8" in thickness. A normal cake may appear cracked or crumbled. If the cartridge is damaged, the cake may shrink in size. Do not use the cartridge if it appears damaged or the cake is substantially reduced in size.

Parenteral drug products should be inspected visually for particulate matter and discoloration prior to administration. The reconstituted solution may initially appear cloudy due to small air bubbles. Do not use the solution if it remains cloudy, contains precipitates, or is discolored.

CAUTION: Do not reuse any solution remaining in the cartridge due to the possibility of bacterial contamination.

Administration

edex® is given as an intracavernous injection over a 5- to 10-second interval. See patient information for edex®.

Stability

The single-dose, dual-chamber cartridge should be reconstituted only when it is certain that the patient is ready to administer the drug. The reconstituted drug solution should be used immediately after reconstitution. Any solution remaining in the cartridge should be discarded.

HOW SUPPLIED

edex® (alprostadil for injection) is available in single-dose, dual-chamber cartridges intended for use with the reusable edex® injection device. One chamber of the cartridge contains 10.75, 21.5, or 43 mcg of alprostadil as a white, sterile, lyophilized powder. The other chamber contains 1.075 mL of sterile 0.9% sodium chloride. When the cartridge is placed into the edex® injection device and reconstituted, the deliverable amount of alprostadil in each milliliter is 10, 20, or 40 mcg, respectively. edex® Cartridge 2 Pack contains one reusable edex® injection device, two single-dose, dual-chamber cartridges, two ½-inch, 29-gauge (0.33 mm × 12.7 mm) needles, and four alcohol swabs. edex® Cartridge 6 Pack contains one reusable edex® injection device, six single-dose, dual-chamber cartridges, six ½-inch, 29-gauge (0.33 mm × 12.7 mm) needles, and twelve alcohol swabs.

The edex® cartridges are supplied in the following packages:

edex® Cartridge 2 Pack (includes one injection device, two cartridges, two needles and four alcohol swabs)
10 mcg | 1 × 2 Pack | NDC 52244-010-02
20 mcg | 1 × 2 Pack | NDC 52244-020-02
40 mcg | 1 × 2 Pack | NDC 52244-040-02

edex® Cartridge 6 Pack (includes one injection device, six cartridges, six needles and twelve alcohol swabs)
10 mcg | 1 × 6 Pack | NDC 52244-010-06
20 mcg | 1 × 6 Pack | NDC 52244-020-06
40 mcg | 1 × 6 Pack | NDC 52244-040-06

STORAGE AND HANDLING

Store at 25°C (77°F); excursions permitted between 15°C - 30°C (59°F - 86°F).

For more information, call Endo at 1-800-462-3636.

Manufactured for:
Endo USA
Malvern, PA 19355

Revised: March 2024

PATIENT INFORMATION

edex®
(alprostadil for injection)
For Intracavernous Use Only
Sterile Powder and Diluent (sterile 0.9% sodium chloride) in Cartridges
PATIENT INFORMATION FOR edex® CARTRIDGES
Please read carefully before using.

Rx Only

Please read carefully before using.

edex® can only be obtained with a prescription from your doctor. You or your partner should be fully trained on the proper injection technique before using edex® at home. Be sure to use only the dose prescribed by your doctor.

This leaflet provides a summary of information about your medicine. Please read this information carefully before you prepare the edex® solution. The reusable edex® injection device is used to prepare and administer the edex® solution. A convenient carrying case is provided for the reusable edex® injection device.

Carefully follow the instructions for administration which are described below. For further information or advice, ask your doctor or pharmacist.

Please keep this information in case you need to refer to it again.

Erectile Dysfunction: Causes and Treatments

There are several causes of erectile dysfunction, commonly known as impotence. These include impaired blood circulation in the penis, nerve damage, hormonal imbalances, excessive alcohol use, emotional problems, and certain medications that you may be taking for other conditions. Smoking has an adverse effect on erectile function by accentuating the effects of other risk factors such as blood vessel disease or high blood pressure. Erectile dysfunction is often due to more than one of these causes.

Treatment for erectile dysfunction includes penile injections, medical devices that produce an erection, surgical procedures (e.g. penile bypass or implants), hormone treatment, psychological counseling, lifestyle changes, or a change in medication. You should not stop taking any prescription medications, unless told to do so by your doctor.

Your doctor has prescribed edex®, a penile injection, to treat your erectile dysfunction.

Use of edex®

edex® is injected into a specific area of the penis (see injection directions below) and should produce an erection in 5 to 20 minutes. The erection can be expected to last up to one hour. You should not use edex® more than 3 times a week. Injections should be administered at least 24 hours apart.

Ideally, the injection should be administered just prior to foreplay. If your partner experiences insufficient vaginal lubrication or painful vaginal sensations during intercourse, the use of a lubricant may be helpful.

Who should NOT use edex®?

Men who have conditions that might result in long-lasting erections should not use edex®. Some of these conditions include sickle cell anemia or trait, leukemia, and tumor of the bone marrow (multiple myeloma). If you have any of these conditions, consult your doctor.

Men with penile implants, severe penile curvature, or those who have been advised not to engage in sexual activity should not use edex®.

edex® should not be used by women or children.

What are the risks of using edex®?

Erections that last more than 6 hours can cause serious damage to the penile tissue and may result in permanent impotence. Call the prescribing physician or, if unavailable, seek professional help immediately if you still have an erection 6 hours after injection. Various treatment options for reversing a prolonged erection are available.

A common side effect of edex® is mild to moderate pain during injection. The erection may also be associated with a painful sensation. If you experience severe pain, contact the prescribing physician.

Call your doctor if you notice any redness, lumps, swelling, tenderness or curvature of the erect penis.

A small amount of bleeding at the injection site may occur. To prevent bruising, apply firm pressure to the injection site for 5 minutes. Tell your doctor if you have a condition or are taking a medicine that interferes with blood clotting.

There is a possibility of needle breakage with use of edex®. To best avoid breaking the needle, you should pay careful attention to your doctor's instructions and try to handle the injection device properly. If the needle breaks during injection and you are able to see and grasp the broken end, you should remove it and contact your doctor. If you cannot see or cannot grasp the broken end, you should promptly contact your doctor.

NOTE: edex® offers no protection from the transmission of sexually transmitted diseases such as HIV (the virus that causes AIDS). Small amounts of bleeding at the injection site can increase the risk of transmission of blood-borne diseases between partners.

There is no approved injectable treatment using multiple medications. In addition, there are no data on the efficacy and safety of these combinations.

edex® Cartridge 2 Pack contains enough supplies for two injections. The 2 Pack contains the following items:

One reusable edex® injection device

One reusable carrying case

Two single-dose, dual-chamber cartridges (one per injection)

Two &frac12;-inch, 29-gauge (0.33 mm x 12.7 mm) sterile needles (one per injection)

Four alcohol swabs (two per injection)

Patient Information for edex® Cartridges

edex® Cartridge 6 Pack contains enough supplies for six injections. The 6 Pack contains the following items:

One reusable edex® injection device

One reusable carrying case

Six single-dose, dual-chamber cartridges (one per injection)

Six &frac12;-inch, 29-gauge (0.33 mm x 12.7 mm) sterile needles (one per injection)

Twelve alcohol swabs (two per injection)

Patient Information for edex® Cartridges

Storage and Handling

1. Store at 25°C (77°F); temperature variations between 15°C - 30°C (59°F - 86°F) are allowed. As with any drug product, extremes in temperature should be avoided. When traveling, do not store in checked luggage during air travel or leave in a closed automobile.

2. edex® solution should be used immediately after reconstitution.

IMPORTANT: To maintain sterility and avoid contamination, follow these directions carefully. Each needle and cartridge should be used only once. Safely discard the supplies (see the “Discard Injection Supplies” section of these instructions). The edex® cartridges contain a solid layer or cake of dry white powder approximately 3/8” in thickness. A normal cake may appear cracked or crumbled. If the cartridge is damaged, the cake may shrink in size. Do not use the cartridge if it appears damaged or the cake is substantially reduced in size.

Self-Injection Procedure

Before using edex®, you should be properly trained by your doctor. Mix edex® just prior to injection. Your dose has been customized for your individual needs. Use only the dose prescribed by your doctor. Have a clean area available to assemble the items necessary for your edex® injection. The reusable edex® injection device is for use only with the single-dose, dual-chamber cartridges and needles included in the edex® Cartridge 2 Pack or 6 Pack.

READ THE INSTRUCTIONS COMPLETELY BEFORE STARTING YOUR SELF-INJECTION PROCEDURE

Prepare edex® Solution

1. Wash your hands thoroughly with soap and water and dry them with a clean towel.

2. Check to see if the seal on the base of the needle is intact. Remove the seal from the base of the needle. Do not touch the exposed needle (Figure B).

3. Attach the needle to the tip of the edex® injection device by turning clockwise until tight (Figure C). Note: Always attach the needle to the injection device before inserting the cartridge into the injection device.

4. Turn the blue portion of the plunger counterclockwise to unscrew it from the injection device (Figure D).

5. Pick up the cartridge and wipe the tip of the cartridge with an alcohol swab. Do not touch the tip of the cartridge after it has been cleansed with the alcohol swab (Figure E).

6. Insert the cartridge into the injection device with the tip facing toward the attached needle (Figure F). The ridge on the cartridge will need to fit into the groove on the injection device.

7. Attach the plunger to the injection device by turning the blue portion of the plunger clockwise until tight (Figure G).

8. Hold the injection device in an upright position with the needle pointing up.

9. To prepare the drug solution, slowly push the plunger until the two gray rubber stoppers touch (Figure H). Gently move the injection device in a back and forth motion until the drug has dissolved and the solution is clear. The solution may initially appear cloudy due to small air bubbles. Do not use the solution if it remains cloudy, is colored, or contains particles.

10. While holding the injection device with the needle pointing up, carefully remove the external and internal protective caps from the needle by pulling them straight off (Figure I). Do not turn the protective caps counterclockwise as this will loosen the needle. Do not discard the large external protective cap; you will need to use it later. Do not touch the exposed needle or allow the needle to touch anything.

11. Gently tap the cartridge so that air bubbles float to the top of the solution (Figure J). Carefully push the plunger until a drop of solution appears at the end of the needle (Figure K).

Note: The plunger pushes the rubber stoppers forward; the rubber stoppers cannot be pulled back with the plunger.

12. Push the plunger until the upper rim of the top stopper reaches the correct volume mark for your prescribed dose. Excess solution will be expelled through the needle.

13. Set the injection device down on a clean, level surface and do not allow the needle to touch anything.

Select Injection Site

14. Choose an injection site mid-shaft on one side of the penis. Avoid visible blood vessels. With each use of edex®, alternate the side of the penis and vary the site of the injection (Figure L). If your penis is not circumcised, pull the foreskin back. Grasping the head of the penis with your thumb and forefinger, stretch it lengthwise along your thigh so that you can clearly see the selected injection site. Wipe the injection site with a new alcohol swab. Do not discard this swab; you will need to use it later.

Inject edex®

15. Pick up the injection device and reposition the penis as in Step 14 to keep it from moving during the injection.

16. Hold the injection device as shown in Figure M. Do not touch the plunger at this time. Position the needle horizontally and gently insert the needle into the selected injection site until the needle is almost completely inserted into the penis (Figure M). Now place your thumb on the plunger and inject the solution slowly over a period of 5 to 10 seconds (Figure N).

17. If the solution does not inject easily, or if you immediately experience a burning pain at the injection site, reposition the needle by advancing it slightly or by partially withdrawing it until the solution can be injected easily and painlessly.

18. Withdraw needle from penis. Immediately apply firm but gentle pressure with the alcohol swab to the injection site for five minutes to prevent bruising (Figure O). Continue to apply firm pressure until bleeding stops. If bleeding continues or recurs after applying pressure, abstain from intercourse.

Discard Injection Supplies

19. Carefully place the large external protective cap on the needle. Remove the needle from the injection device by turning counterclockwise.

20. Remove the cartridge from the injection device by turning the blue portion of the plunger counterclockwise.

21. Discard your needle in a special container for disposal of sharp medical supplies. Ask your doctor or pharmacist where you can obtain these special containers. Follow the directions on your disposal container for proper disposal procedures. Do not reuse or share needles.

22. Clean the reusable injection device with warm water and a mild soap after each use. Once the injection device is dry, place it in the carrying case.

As with all prescription medicines, do not allow anyone else to use your medication. Proper injection technique and individual dose titration are essential for the safe use of this product.

Manufactured for:
Endo USA
Malvern, PA 19355

Revised: March 2024